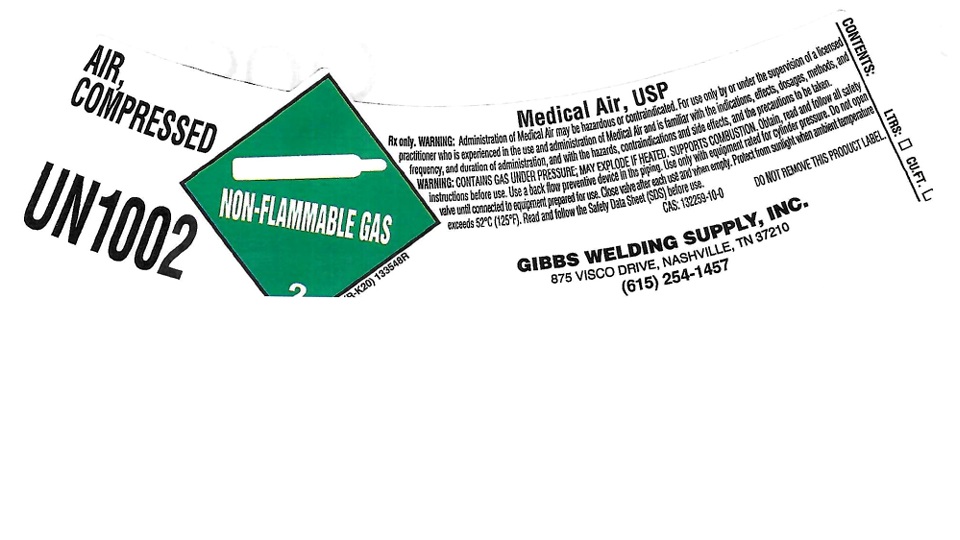 DRUG LABEL: Air
NDC: 58632-003 | Form: GAS
Manufacturer: GIBBS WELDING SUPPLY, INC.
Category: prescription | Type: HUMAN PRESCRIPTION DRUG LABEL
Date: 20251008

ACTIVE INGREDIENTS: AIR 1000 mL/1 L

Air

PACKAGE LABEL

AIR, COMPRESSED

UN1002

Medical Air, USP

Rx only. WARNING: Administration of Medical Air may be hazardous or contraindicated. For use only by or under the supervision of a licensed practitioner who is experienced in the use and administration of Medical Air and is familiar with the indications, effects, dosages, methods, and frequency, and duration of administration, and with the hazards, contraindications and side effects, all the precautions to be taken.

WARNING: CONTAINS GAS UNDER PRESSURE; MAY EXPLODE IF HEATED. SUPPORTS COMBUSTIN. Obtain, read and follow all safety instructions before use. Use a back flow preventive device in the piping. Use only with equipment rated for cylinder pressure. Do not open valve until connected to equipment prepared for use. Close valve after each use and when empty. Protect from sunlight when ambient temperature exceeds 52 C (125 F). Read and follow the Safety Data Sheet (SDS) before use.

CAS: 132259-10-0 DO NOT REMOVE THIS PRODUCT LABEL.

GIBBS WELDING SUPPLY, INC.

875 VISCO DRIVE, NASHVILLE, TN 37210

(615) 254-1457

CONTENTS: LTRS: CU.FT